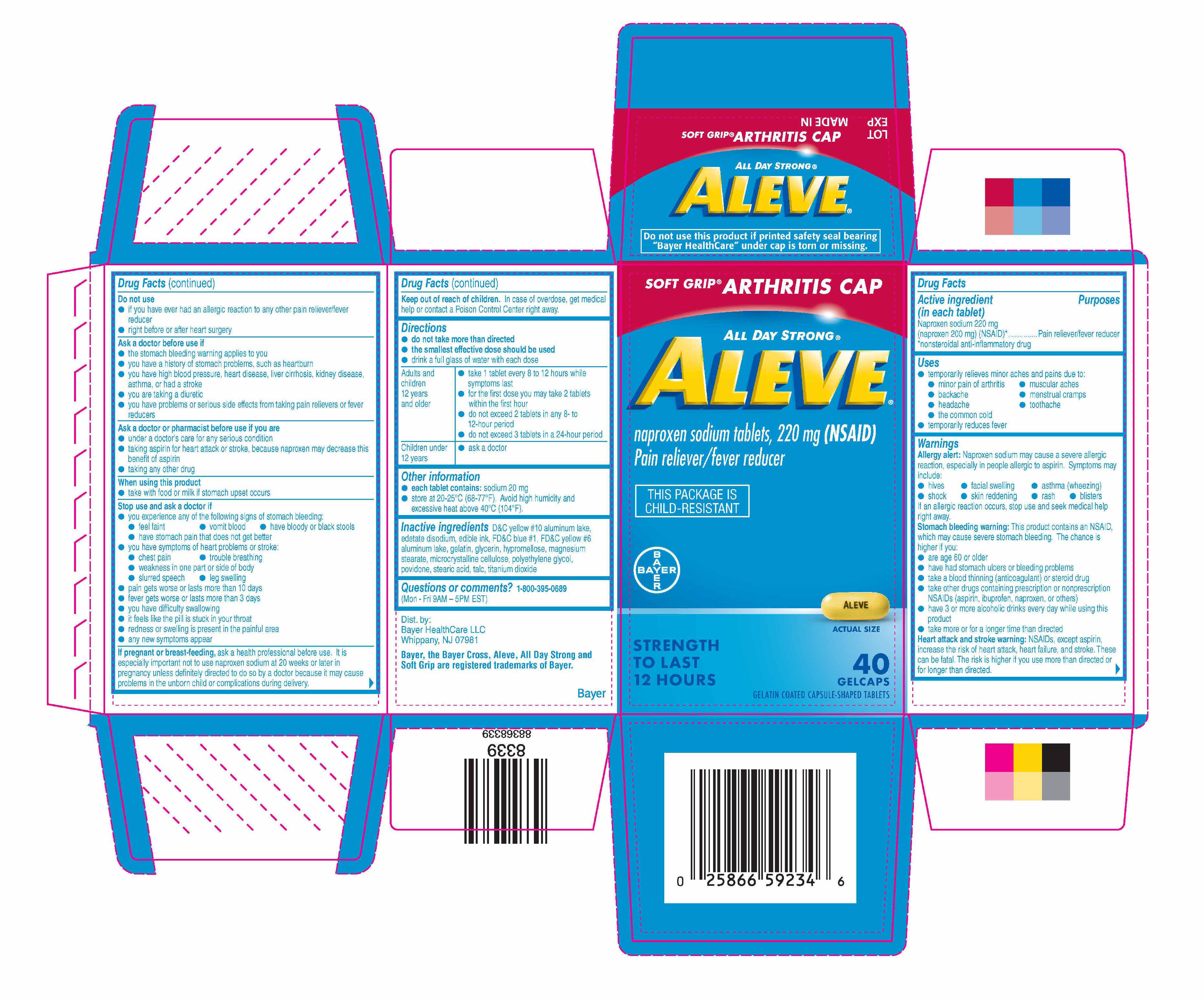 DRUG LABEL: Aleve
NDC: 0280-6070 | Form: TABLET, COATED
Manufacturer: Bayer HealthCare LLC.
Category: otc | Type: HUMAN OTC DRUG LABEL
Date: 20251204

ACTIVE INGREDIENTS: NAPROXEN SODIUM 220 mg/1 1
INACTIVE INGREDIENTS: ALUMINUM OXIDE; D&C YELLOW NO. 10; EDETATE DISODIUM; FD&C BLUE NO. 1; FD&C YELLOW NO. 6; GELATIN; GLYCERIN; HYPROMELLOSES; MAGNESIUM STEARATE; CELLULOSE, MICROCRYSTALLINE; POLYETHYLENE GLYCOL, UNSPECIFIED; POVIDONE; STEARIC ACID; TALC; TITANIUM DIOXIDE

Aleve®
Gelcaps

Drug Facts

Active ingredient (in each tablet)

Naproxen sodium 220 mg (naproxen 200 mg) (NSAID) [nonsteroidal anti-inflammatory drug]

Purpose

Pain reliever/fever reducer

Uses

- temporarily relieves minor aches and pains due to:
  - minor pain of arthritis
  - muscular aches
  - backache
  - menstrual cramps
  - headache
  - toothache
  - the common cold
- temporarily reduces fever

Directions

- do not take more than directed
- the smallest effective dose should be used
- drink a full glass of water with each dose

Adults and children 12 years and older | - take 1 tablet every 8 to 12 hours while symptoms last - for the first dose you may take 2 tablets within the first hour - do not exceed 2 tablets in any 8- to 12-hour period - do not exceed 3 tablets in a 24-hour period
Children under 12 years | - ask a doctor

Other information

- each tablet contains: sodium 20 mg
- store at 20-25°C (68-77°F). Avoid high humidity and excessive heat above 40°C (104°F).

Inactive ingredients

D&C yellow #10 aluminum lake, edetate disodium, edible ink, FD&C blue #1, FD&C yellow #6 aluminum lake, gelatin, glycerin, hypromellose, magnesium stearate, microcrystalline cellulose, polyethylene glycol, povidone, stearic acid, talc, titanium dioxide

Questions or comments?

1-800-395-0689 (Mon - Fri 9AM - 5PM EST)

Dist. by :

Bayer Healthcare LLC

Whippany, NJ 07981

PRINCIPAL DISPLAY PANEL

SOFT GRIP® ARTHRITIS CAP

ALL DAY STRONG®

ALEVE®

naproxen sodium tablets, 220 mg (NSAID)

Pain reliever/fever reducer

THIS PACKAGE IS

CHILD-RESISTANT

STRENGTH

TO LAST

12 HOURS

40 GELCAPS

GELATIN COATED

CAPSULE-SHAPED TABLETS